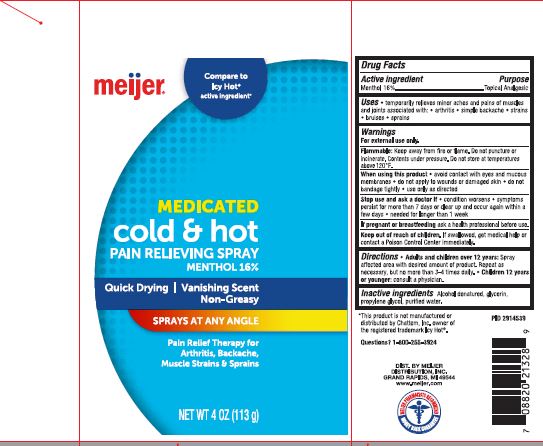 DRUG LABEL: Meijer Medicated Cold and Hot Pain Relieving
NDC: 52313-1110 | Form: SPRAY
Manufacturer: Sklar BOV Solutions Inc
Category: otc | Type: HUMAN OTC DRUG LABEL
Date: 20220131

ACTIVE INGREDIENTS: MENTHOL 160 mg/1 g
INACTIVE INGREDIENTS: WATER; ALCOHOL; GLYCERIN

Meijer Medicated Cp;d amd hot Pain Relieving

Use

Temporarly releaves minor aches and pains of muscles and joints associated wotj artjrotos, , simple backaches, strains, bruses,

and sprains

Active Ingredient Purpose

Menthol 16% Topical Analgesic

Warnings

For external use only

Flammable

Keep away for from fire or flame. Do not puncture or incinerate.

Contents under pressure. Do not store at temperatures above 120ºF.

When using this product, avoid contact with eyes and mucouse membranes.

Do not apply to wounds or damaged skin

Do not bandage tightly

Use only as directed

Stop use and ask a doctor if condition worsens, symptoms presist for more than 7 days, or clears up and occur again within

a few days.

needed for more that a weekl

If pregnant or breastfeeding ask a health professional before use.

DOSAGE AND ADMINISTRATION

Directions , Adults and Children over 12 years old

Spray affected area with desired amount of product,

Repeat at needed but no more that 3 - 4 times dailiy

Children 12 years of younger.

Consult a physician

Inactive Ingredients

Alcohol denat. glycerin, propylene glycol, water

KEEP OUT OF REACH OF CHILDREN

Keep our of reach of Children. If ingested get medical help or contact a Poison Control Center immediatly

Questions 1-800-255-3924

PACKAGE LABEL

113 g NDC52313-1110 Meijer Medicated Cold & Hot Pain Relieving

Menthol 16%

Quick Drying | Vanishing Scent

Non-Greasy

Sprays at any angle

Pain Relief Therapy for

Arthritis, Backache

Muscle Strains and Springs